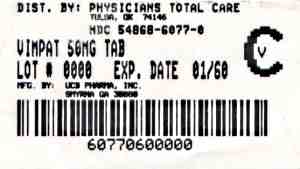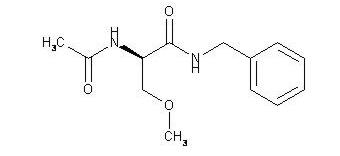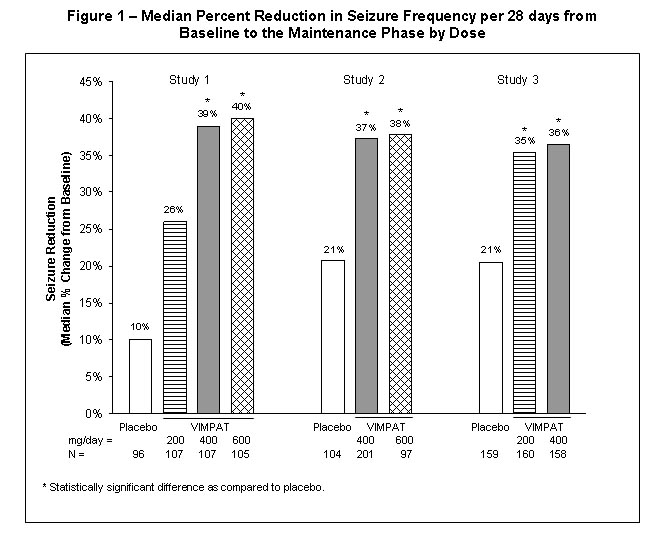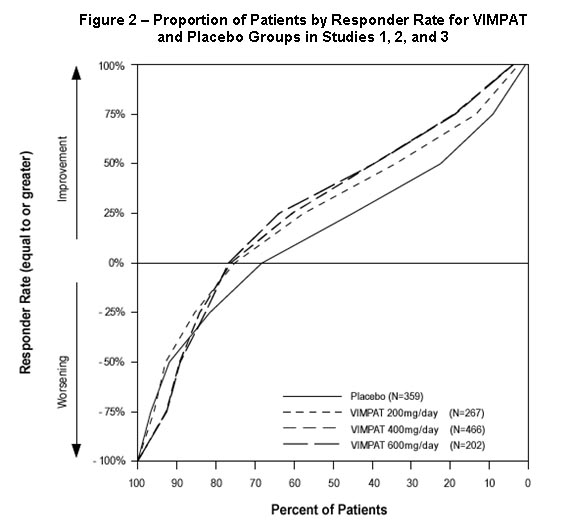 DRUG LABEL: Vimpat
NDC: 54868-6077 | Form: TABLET, FILM COATED
Manufacturer: Physicians Total Care, Inc.
Category: prescription | Type: HUMAN PRESCRIPTION DRUG LABEL
Date: 20120112
DEA Schedule: CV

ACTIVE INGREDIENTS: lacosamide 50 mg/1 1
INACTIVE INGREDIENTS: silicon dioxide; crospovidone; hydroxypropyl cellulose; hypromelloses; magnesium stearate; cellulose, microcrystalline; polyethylene glycols; polyvinyl alcohol; talc; titanium dioxide; ferric oxide red; ferrosoferric oxide; FD&C Blue NO. 2; indigotindisulfonate sodium; aluminum oxide

HIGHLIGHTS OF PRESCRIBING INFORMATION

These highlights do not include all the information needed to use VIMPAT® safely and effectively. See full prescribing information for VIMPAT.
VIMPAT® (lacosamide) Tablet, Film Coated for Oral use, CV
VIMPAT® (lacosamide) Injection for Intravenous use, CV
VIMPAT® (lacosamide) Oral Solution, CV
Initial U.S. Approval: 2008

1 INDICATIONS AND USAGE

VIMPAT is indicated for:

- Partial-onset seizures (1.1): Tablets and oral solution are indicated for adjunctive therapy in patients ≥17 years. Injection is indicated as short term replacement when oral administration is not feasible in these patients.

2 DOSAGE AND ADMINISTRATION

- Partial-onset seizures (2.1): Initially, give 50 mg twice daily (100 mg/day). The dose may be increased, based on clinical response and tolerability, at weekly intervals by 100 mg/day given as two divided doses to a daily dose of 200 to 400 mg/day. VIMPAT injection may be given without further dilution or mixed in compatible diluent and should be administered intravenously over a period of 30 to 60 minutes. (2.1)
- Oral-Intravenous Replacement therapy (2.1): When switching from oral VIMPAT, the initial total daily intravenous dosage of VIMPAT should be equivalent to the total daily dosage and frequency of oral VIMPAT. At the end of the intravenous treatment period, the patient may be switched to VIMPAT oral administration at the equivalent daily dosage and frequency of the intravenous administration.
  See full prescribing information for compatibility and stability (2.1) and dosing in patients with renal impairment (2.2) and hepatic impairment (2.3).

3 DOSAGE FORMS AND STRENGTHS

- 50 mg (pink), 100 mg (dark yellow), 150 mg (salmon), 200 mg (blue) film-coated tablets (3)
- 200 mg/20 mL single-use vial for intravenous use (3)
- 10 mg/mL oral solution (3)

4 CONTRAINDICATIONS

- None

5 WARNINGS AND PRECAUTIONS

- Suicidal Behavior and Ideation (5.1)
- Patients should be advised that VIMPAT may cause dizziness and ataxia. (5.2)
- Caution is advised for patients with known cardiac conduction problems [e.g., second-degree atrioventricular (AV) block], who are taking drugs known to induce PR interval prolongation, or with severe cardiac disease such as myocardial ischemia or heart failure. (5.3)
- Patients should be advised that VIMPAT may cause syncope. (5.4)
- In patients with seizure disorders, VIMPAT should be gradually withdrawn to minimize the potential of increased seizure frequency. (5.5)
- Multiorgan Hypersensitivity Reactions (5.6)
- Phenylketonurics (5.7)

6 ADVERSE REACTIONS

Most common adverse reactions (≥10% and greater than placebo) are diplopia, headache, dizziness, nausea (6.1)

To report SUSPECTED ADVERSE REACTIONS, contact UCB, Inc. at 1-800-477-7877 or FDA at 1-800-FDA-1088 or www.fda.gov/medwatch

8 USE IN SPECIFIC POPULATIONS

- To enroll in the UCB AED Pregnancy Registry call 1-888-537-7734 (toll free).To enroll in the North American Antiepileptic Drug Pregnancy Registry call 1-888-233-2334 (toll free). (8.1)
- Renal impairment: Dose adjustment is recommended for patients with severe renal impairment (creatinine clearance ≤ 30 mL/min). Dose supplementation should be considered following hemodialysis. (12.3)
- Hepatic impairment: Dose adjustment is recommended for patients with mild or moderate hepatic impairment. Use in severe hepatic impairment patients is not recommended. Patients with co-existing hepatic and renal impairment should be monitored closely during dose titration. (12.3)

FULL PRESCRIBING INFORMATION

1 INDICATIONS AND USAGE

1.1 Partial-Onset Seizures

VIMPAT (lacosamide) tablets and oral solution are indicated as adjunctive therapy in the treatment of partial-onset seizures in patients with epilepsy aged 17 years and older.

VIMPAT (lacosamide) injection for intravenous use is indicated as adjunctive therapy in the treatment of partial-onset seizures in patients with epilepsy aged 17 years and older when oral administration is temporarily not feasible.

2 DOSAGE AND ADMINISTRATION

VIMPAT may be taken with or without food.

When using VIMPAT oral solution, it is recommended that a calibrated measuring device be obtained and used. A household teaspoon or tablespoon is not an adequate measuring device. Healthcare providers should recommend a device that can measure and deliver the prescribed dose accurately, and provide instructions for measuring the dosage.

2.1 Partial-Onset Seizures

VIMPAT can be initiated with either oral or intravenous administration. The initial dose should be 50 mg twice daily (100 mg per day). VIMPAT can be increased at weekly intervals by 100 mg/day given as two divided doses up to the recommended maintenance dose of 200 to 400 mg/day, based on individual patient response and tolerability. In clinical trials, the 600 mg daily dose was not more effective than the 400 mg daily dose, and was associated with a substantially higher rate of adverse reactions. [see Clinical Studies (14.1)]

Switching from Oral to Intravenous Dosing

When switching from oral VIMPAT, the initial total daily intravenous dosage of VIMPAT should be equivalent to the total daily dosage and frequency of oral VIMPAT and should be infused intravenously over a period of 30 to 60 minutes. There is experience with twice daily intravenous infusion for up to 5 days.

Switching from Intravenous to Oral Dosing

At the end of the intravenous treatment period, the patient may be switched to VIMPAT oral administration at the equivalent daily dosage and frequency of the intravenous administration.

Compatibility and Stability

VIMPAT injection can be administered intravenously without further dilution or may be mixed with diluents. VIMPAT injection was found to be physically compatible and chemically stable when mixed with the following diluents for at least 24 hours and stored in glass or polyvinyl chloride (PVC) bags at ambient room temperature 15-30°C (59-86°F).

Diluents:

Sodium Chloride Injection 0.9% (w/v)
Dextrose Injection 5% (w/v)
Lactated Ringer's Injection

The stability of VIMPAT injection in other infusion solutions has not been evaluated. Product with particulate matter or discoloration should not be used.

Any unused portion of VIMPAT injection should be discarded.

2.2 Patients with Renal Impairment

No dose adjustment is necessary in patients with mild to moderate renal impairment. A maximum dose of 300 mg/day VIMPAT is recommended for patients with severe renal impairment [creatinine clearance (CLCR) ≤30mL/min] and in patients with endstage renal disease. VIMPAT is effectively removed from plasma by hemodialysis. Following a 4-hour hemodialysis treatment, dosage supplementation of up to 50% should be considered. In all renally impaired patients, the dose titration should be performed with caution. [see Use in Specific Populations (8.6)]

2.3 Patients with Hepatic Impairment

The dose titration should be performed with caution in patients with hepatic impairment. A maximum dose of 300 mg/day is recommended for patients with mild or moderate hepatic impairment.

VIMPAT use is not recommended in patients with severe hepatic impairment [see Use in Specific Populations (8.7)].

3 DOSAGE FORMS AND STRENGTHS

50 mg (pink), 100 mg (dark yellow), 150 mg (salmon), and 200 mg (blue) film-coated tablets

200 mg/20mL injection

10 mg/mL oral solution

4 CONTRAINDICATIONS

None.

5 WARNINGS AND PRECAUTIONS

5.1 Suicidal Behavior and Ideation

Antiepileptic drugs (AEDs), including VIMPAT, increase the risk of suicidal thoughts or behavior in patients taking these drugs for any indication. Patients treated with any AED for any indication should be monitored for the emergence or worsening of depression, suicidal thoughts or behavior, and/or any unusual changes in mood or behavior.

Pooled analyses of 199 placebo-controlled clinical trials (mono- and adjunctive therapy) of 11 different AEDs showed that patients randomized to one of the AEDs had approximately twice the risk (adjusted Relative Risk 1.8, 95% CI:1.2, 2.7) of suicidal thinking or behavior compared to patients randomized to placebo. In these trials, which had a median treatment duration of 12 weeks, the estimated incidence of suicidal behavior or ideation among 27,863 AED-treated patients was 0.43%, compared to 0.24% among 16,029 placebo-treated patients, representing an increase of approximately one case of suicidal thinking or behavior for every 530 patients treated. There were four suicides in drug-treated patients in the trials and none in placebo-treated patients, but the number of events is too small to allow any conclusion about drug effect on suicide.

The increased risk of suicidal thoughts or behavior with AEDs was observed as early as one week after starting treatment with AEDs and persisted for the duration of treatment assessed. Because most trials included in the analysis did not extend beyond 24 weeks, the risk of suicidal thoughts or behavior beyond 24 weeks could not be assessed.

The risk of suicidal thoughts or behavior was generally consistent among drugs in the data analyzed. The finding of increased risk with AEDs of varying mechanisms of action and across a range of indications suggests that the risk applies to all AEDs used for any indication. The risk did not vary substantially by age (5-100 years) in the clinical trials analyzed.

Table 1 shows absolute and relative risk by indication for all evaluated AEDs.

Table 1 Risk by indication for antiepileptic drugs in the pooled analysis
Indication | Placebo Patients with Events Per 1000 Patients | Drug Patients with Events Per 1000 Patients | Relative Risk: Incidence of Events in Drug Patients/Incidence in Placebo Patients | Risk Difference: Additional Drug Patients with Events Per 1000 Patients
Epilepsy | 1.0 | 3.4 | 3.5 | 2.4
Psychiatric | 5.7 | 8.5 | 1.5 | 2.9
Other | 1.0 | 1.8 | 1.9 | 0.9
Total | 2.4 | 4.3 | 1.8 | 1.9

The relative risk for suicidal thoughts or behavior was higher in clinical trials for epilepsy than in clinical trials for psychiatric or other conditions, but the absolute risk differences were similar.

Anyone considering prescribing VIMPAT or any other AED must balance this risk with the risk of untreated illness. Epilepsy and many other illnesses for which antiepileptics are prescribed are themselves associated with morbidity and mortality and an increased risk of suicidal thoughts and behavior. Should suicidal thoughts and behavior emerge during treatment, the prescriber needs to consider whether the emergence of these symptoms in any given patient may be related to the illness being treated.

Patients, their caregivers, and families should be informed that AEDs increase the risk of suicidal thoughts and behavior and should be advised of the need to be alert for the emergence or worsening of the signs and symptoms of depression, any unusual changes in mood or behavior, or the emergence of suicidal thoughts, behavior, or thoughts about self-harm. Behaviors of concern should be reported immediately to healthcare providers.

5.2 Dizziness and Ataxia

Patients should be advised that VIMPAT may cause dizziness and ataxia. Accordingly, they should be advised not to drive a car or to operate other complex machinery until they are familiar with the effects of VIMPAT on their ability to perform such activities.

In patients with partial-onset seizures taking 1 to 3 concomitant AEDs, dizziness was experienced by 25% of patients randomized to the recommended doses (200 to 400 mg/day) of VIMPAT (compared with 8% of placebo patients) and was the adverse event most frequently leading to discontinuation (3%). Ataxia was experienced by 6% of patients randomized to the recommended doses (200 to 400 mg/day) of VIMPAT (compared to 2% of placebo patients). The onset of dizziness and ataxia was most commonly observed during titration. There was a substantial increase in these adverse events at doses higher than 400 mg/day. [see Adverse Reactions/Table 2 (6.1)]

5.3 Cardiac Rhythm and Conduction Abnormalities

PR interval prolongation

Dose-dependent prolongations in PR interval with VIMPAT have been observed in clinical studies in patients and in healthy volunteers. [see Clinical Pharmacology (12.2)] In clinical trials in patients with partial-onset epilepsy, asymptomatic first-degree atrioventricular (AV) block was observed as an adverse reaction in 0.4% (4/944) of patients randomized to receive VIMPAT and 0% (0/364) of patients randomized to receive placebo. In clinical trials in patients with diabetic neuropathy, asymptomatic first-degree AV block was observed as an adverse reaction in 0.5% (5/1023) of patients receiving VIMPAT and 0% (0/291) of patients receiving placebo. Second degree or higher AV block has been reported in postmarketing experience in epilepsy patients. When VIMPAT is given with other drugs that prolong the PR interval, further PR prolongation is possible. Patients should be made aware of the symptoms of second-degree or higher AV block (e.g. slow or irregular pulse, feeling of lightheadedness and fainting) and told to contact their physician should any of these occur.

VIMPAT should be used with caution in patients with known conduction problems (e.g. marked first-degree AV block, second-degree or higher AV block and sick sinus syndrome without pacemaker), or with severe cardiac disease such as myocardial ischemia or heart failure. In such patients, obtaining an ECG before beginning VIMPAT, and after VIMPAT is titrated to steady-state, is recommended.

Atrial fibrillation and Atrial flutter

In the short-term investigational trials of VIMPAT in epilepsy patients, there were no cases of atrial fibrillation or flutter, however, both have been reported in open label epilepsy trials and in postmarketing experience. In patients with diabetic neuropathy, 0.5% of patients treated with VIMPAT experienced an adverse reaction of atrial fibrillation or atrial flutter, compared to 0% of placebo-treated patients. VIMPAT administration may predispose to atrial arrhythmias (atrial fibrillation or flutter), especially in patients with diabetic neuropathy and/or cardiovascular disease. Patients should be made aware of the symptoms of atrial fibrillation and flutter (e.g., palpitations, rapid pulse, shortness of breath) and told to contact their physician should any of these symptoms occur.

5.4 Syncope

In the short-term controlled trials of VIMPAT in epilepsy patients with no significant system illnesses, there was no increase in syncope compared to placebo. In the short-term controlled trials of VIMPAT in patients with diabetic neuropathy, 1.2% of patients who were treated with VIMPAT reported an adverse reaction of syncope or loss of consciousness, compared to 0% of placebo-treated patients with diabetic neuropathy. Most of the cases of syncope were observed in patients receiving doses above 400 mg/day. The cause of syncope was not determined in most cases. However, several were associated with either changes in orthostatic blood pressure, atrial flutter/fibrillation (and associated tachycardia), or bradycardia.

5.5 Withdrawal of Antiepileptic Drugs (AEDs)

As with all AEDs, VIMPAT should be withdrawn gradually (over a minimum of 1 week) to minimize the potential of increased seizure frequency in patients with seizure disorders.

5.6 Multiorgan Hypersensitivity Reactions

One case of symptomatic hepatitis and nephritis was observed among 4011 subjects exposed to VIMPAT during clinical development. The event occurred in a healthy volunteer, 10 days after stopping VIMPAT treatment. The subject was not taking any concomitant medication and potential known viral etiologies for hepatitis were ruled out. The subject fully recovered within a month, without specific treatment. The case is consistent with a delayed multiorgan hypersensitivity reaction. Additional potential cases included 2 with rash and elevated liver enzymes and 1 with myocarditis and hepatitis of uncertain etiology.

Multiorgan hypersensitivity reactions (also known as Drug Reaction with Eosinophilia and Systemic Symptoms, or DRESS) have been reported with other anticonvulsants and typically, although not exclusively, present with fever and rash associated with other organ system involvement, that may or may not include eosinophilia, hepatitis, nephritis, lymphadenopathy, and/or myocarditis. Because this disorder is variable in its expression, other organ system signs and symptoms not noted here may occur. If this reaction is suspected, VIMPAT should be discontinued and alternative treatment started.

5.7 Phenylketonurics

VIMPAT oral solution contains aspartame, a source of phenylalanine. A 200 mg dose of VIMPAT oral solution (equivalent to 20 mL) contains 0.32 mg of phenylalanine.

6 ADVERSE REACTIONS

Because clinical trials are conducted under widely varying conditions, adverse reaction rates observed in the clinical trials of a drug cannot be directly compared to rates in the clinical trials of another drug and may not reflect the rates observed in practice.

In all controlled and uncontrolled trials in patients with partial-onset seizures, 1327 patients have received VIMPAT of whom 1000 have been treated for longer than 6 months and 852 for longer than 12 months.

6.1 Clinical Trials Experience

Controlled Trials

Adverse reactions leading to discontinuation

In controlled clinical trials, the rate of discontinuation as a result of an adverse event was 8% and 17% in patients randomized to receive VIMPAT at the recommended doses of 200 and 400 mg/day, respectively, 29% at 600 mg/day, and 5% in patients randomized to receive placebo. The adverse events most commonly (>1% in the VIMPAT total group and greater than placebo) leading to discontinuation were dizziness, ataxia, vomiting, diplopia, nausea, vertigo, and vision blurred.

Most common adverse reactions

Table 2 gives the incidence of treatment-emergent adverse events that occurred in ≥2% of adult patients with partial-onset seizures in the total VIMPAT group and for which the incidence was greater than placebo. The majority of adverse events in the VIMPAT patients were reported with a maximum intensity of 'mild' or 'moderate'.

Table 2: Treatment-Emergent Adverse Event Incidence in Double-Blind, Placebo-Controlled Partial-Onset Seizure Trials (Events ≥2% of Patients in VIMPAT Total and More Frequent Than in the Placebo Group)
System Organ Class/ Preferred Term | Placebo N=364 % | VIMPAT 200 mg/day N=270 % | VIMPAT 400 mg/day N=471 % | VIMPAT 600 mg/day N=203 % | VIMPAT Total N=944 %
Ear and labyrinth disorder
Vertigo | 1 | 5 | 3 | 4 | 4
Eye disorders
Diplopia | 2 | 6 | 10 | 16 | 11
Vision blurred | 3 | 2 | 9 | 16 | 8
Gastrointestinal disorders
Nausea | 4 | 7 | 11 | 17 | 11
Vomiting | 3 | 6 | 9 | 16 | 9
Diarrhea | 3 | 3 | 5 | 4 | 4
General disorders and administration site conditions
Fatigue | 6 | 7 | 7 | 15 | 9
Gait disturbance | <1 | <1 | 2 | 4 | 2
Asthenia | 1 | 2 | 2 | 4 | 2
Injury, poisoning and procedural complications
Contusion | 3 | 3 | 4 | 2 | 3
Skin laceration | 2 | 2 | 3 | 3 | 3
Nervous system disorders
Dizziness | 8 | 16 | 30 | 53 | 31
Headache | 9 | 11 | 14 | 12 | 13
Ataxia | 2 | 4 | 7 | 15 | 8
Somnolence | 5 | 5 | 8 | 8 | 7
Tremor | 4 | 4 | 6 | 12 | 7
Nystagmus | 4 | 2 | 5 | 10 | 5
Balance disorder | 0 | 1 | 5 | 6 | 4
Memory impairment | 2 | 1 | 2 | 6 | 2
Psychiatric disorders
Depression | 1 | 2 | 2 | 2 | 2
Skin and subcutaneous disorders
Pruritus | 1 | 3 | 2 | 3 | 2

Laboratory abnormalities

Abnormalities in liver function tests have been observed in controlled trials with VIMPAT in adult patients with partial-onset seizures who were taking 1 to 3 concomitant anti-epileptic drugs. Elevations of ALT to ≥3× ULN occurred in 0.7% (7/935) of VIMPAT patients and 0% (0/356) of placebo patients. One case of hepatitis with transaminases >20x ULN was observed in one healthy subject 10 days after VIMPAT treatment completion, along with nephritis (proteinuria and urine casts). Serologic studies were negative for viral hepatitis. Transaminases returned to normal within one month without specific treatment. At the time of this event, bilirubin was normal. The hepatitis/nephritis was interpreted as a delayed hypersensitivity reaction to VIMPAT.

Other Adverse Reactions in Patients with Partial-Onset Seizures

The following is a list of treatment-emergent adverse events reported by patients treated with VIMPAT in all clinical trials in patients with partial-onset seizures, including controlled trials and long-term open-label extension trials. Events addressed in other tables or sections are not listed here. Events included in this list from the controlled trials occurred more frequently on drug than on placebo and were based on consideration of VIMPAT pharmacology, frequency above that expected in the population, seriousness, and likelihood of a relationship to VIMPAT. Events are further classified within system organ class.

Blood and lymphatic system disorders: neutropenia, anemia

Cardiac disorders: palpitations

Ear and labyrinth disorders: tinnitus

Gastrointestinal disorders: constipation, dyspepsia, dry mouth, oral hypoaesthesia

General disorders and administration site conditions: irritability, pyrexia, feeling drunk

Injury, poisoning, and procedural complications: fall

Musculoskeletal and connective tissue disorders: muscle spasms

Nervous system disorders: paresthesia, cognitive disorder, hypoaesthesia, dysarthria, disturbance in attention, cerebellar syndrome

Psychiatric disorders: confusional state, mood altered, depressed mood

Intravenous Adverse Reactions

Adverse reactions with intravenous administration generally appeared similar to those observed with the oral formulation, although intravenous administration was associated with local adverse events such as injection site pain or discomfort (2.5%), irritation (1%), and erythema (0.5%). One case of profound bradycardia (26 bpm: BP 100/60 mmHg) was observed in a patient during a 15 minute infusion of 150mg VIMPAT. This patient was on a beta-blocker. Infusion was discontinued and the patient experienced a rapid recovery.

Comparison of Gender and Race

The overall adverse event rate was similar in male and female patients. Although there were few non-Caucasian patients, no differences in the incidences of adverse events compared to Caucasian patients were observed.

6.2 Postmarketing Experience

The following adverse reactions have been identified during postapproval use of VIMPAT. Because these reactions are reported voluntarily from a population of uncertain size, it is not always possible to reliably estimate their frequency or establish a causal relationship to drug exposure.

Cardiac disorders: Atrioventricular block, atrial fibrillation, atrial flutter, bradycardia

Immune system disorders: Drug hypersensitivity reactions

Psychiatric disorders: Aggression, agitation, insomnia, psychotic disorder

Skin and subcutaneous tissue disorders: Angioedema, rash, urticaria

7 DRUG INTERACTIONS

Drug-drug interaction studies in healthy subjects showed no pharmacokinetic interactions between VIMPAT and carbamazepine, valproate, digoxin, metformin, omeprazole, or an oral contraceptive containing ethinylestradiol and levonorgestrel. There was no evidence for any relevant drug-drug interaction of VIMPAT with common AEDs in the placebo-controlled clinical trials in patients with partial-onset seizures [see Clinical Pharmacology (12.3)].

The lack of pharmacokinetic interaction does not rule out the possibility of pharmacodynamic interactions, particularly among drugs that affect the heart conduction system.

8 USE IN SPECIFIC POPULATIONS

8.1 Pregnancy

Pregnancy Category C

Lacosamide produced developmental toxicity (increased embryofetal and perinatal mortality, growth deficit) in rats following administration during pregnancy. Developmental neurotoxicity was observed in rats following administration during a period of postnatal development corresponding to the third trimester of human pregnancy. These effects were observed at doses associated with clinically relevant plasma exposures.

Lacosamide has been shown in vitro to interfere with the activity of collapsin response mediator protein-2 (CRMP-2), a protein involved in neuronal differentiation and control of axonal outgrowth. Potential adverse effects on CNS development can not be ruled out.

There are no adequate and well-controlled studies in pregnant women. VIMPAT should be used during pregnancy only if the potential benefit justifies the potential risk to the fetus.

Oral administration of lacosamide to pregnant rats (20, 75, or 200 mg/kg/day) and rabbits (6.25, 12.5, or 25 mg/kg/day) during the period of organogenesis did not produce any teratogenic effects. However, the maximum doses evaluated were limited by maternal toxicity in both species and embryofetal death in rats. These doses were associated with maternal plasma lacosamide exposures [area under the plasma-time concentration curve; (AUC)] ≈2 and 1 times (rat and rabbit, respectively) that in humans at the maximum recommended human dose (MRHD) of 400 mg/day.

When lacosamide (25, 70, or 200 mg/kg/day) was orally administered to rats throughout gestation, parturition, and lactation, increased perinatal mortality and decreased body weights were observed in the offspring at the highest dose. The no-effect dose for pre- and post-natal developmental toxicity in rats (70 mg/kg/day) was associated with a maternal plasma lacosamide AUC approximately equal to that in humans at the MRHD.

Oral administration of lacosamide (30, 90, or 180 mg/kg/day) to rats during the neonatal and juvenile periods of postnatal development resulted in decreased brain weights and long-term neurobehavioral changes (altered open field performance, deficits in learning and memory). The early postnatal period in rats is generally thought to correspond to late pregnancy in humans in terms of brain development. The no-effect dose for developmental neurotoxicity in rats was associated with a plasma lacosamide AUC approximately 0.5 times that in humans at the MRHD.

Pregnancy Registry

UCB, Inc. has established the UCB AED Pregnancy Registry to advance scientific knowledge about safety and outcomes in pregnant women being treated with VIMPAT. To ensure broad program access and reach, either a healthcare provider or the patient can initiate enrollment in the UCB AED Pregnancy Registry by calling 1-888-537-7734 (toll free).

Physicians are also advised to recommend that pregnant patients taking VIMPAT enroll in the North American Antiepileptic Drug Pregnancy Registry. This can be done by calling the toll free number 1-888-233-2334, and must be done by patients themselves. Information on the registry can also be found at the website http://www.aedpregnancyregistry.org/.

8.2 Labor and Delivery

The effects of VIMPAT on labor and delivery in pregnant women are unknown. In a pre- and post-natal study in rats, there was a tendency for prolonged gestation in all lacosamide treated groups at plasma exposures (AUC) at or below the plasma AUC in humans at the maximum recommended human dose of 400 mg/day.

8.3 Nursing Mothers

Studies in lactating rats have shown that lacosamide and/or its metabolites are excreted in milk. It is not known whether VIMPAT is excreted in human milk. Because many drugs are excreted into human milk, a decision should be made whether to discontinue nursing or to discontinue VIMPAT, taking into account the importance of the drug to the mother.

8.4 Pediatric Use

The safety and effectiveness of VIMPAT in pediatric patients <17 years have not been established.

Lacosamide has been shown in vitro to interfere with the activity of CRMP-2, a protein involved in neuronal differentiation and control of axonal outgrowth. Potential adverse effects on CNS development can not be ruled out. Administration of lacosamide to rats during the neonatal and juvenile periods of postnatal development resulted in decreased brain weights and long-term neurobehavioral changes (altered open field performance, deficits in learning and memory). The no-effect dose for developmental neurotoxicity in rats was associated with a plasma lacosamide exposure (AUC) approximately 0.5 times the human plasma AUC at the maximum recommended human dose of 400 mg/day.

8.5 Geriatric Use

There were insufficient numbers of elderly patients enrolled in partial-onset seizure trials (n=18) to adequately assess the effectiveness of VIMPAT in this population.

In healthy subjects, the dose and body weight normalized pharmacokinetic parameters AUC and Cmax were approximately 20% higher in elderly subjects compared to young subjects. The slightly higher lacosamide plasma concentrations in elderly subjects are possibly caused by differences in total body water (lean body weight) and age-associated decreased renal clearance. No VIMPAT dose adjustment based on age is considered necessary. Caution should be exercised for dose titration in elderly patients.

8.6 Patients with Renal Impairment

A maximum dose of 300 mg/day is recommended for patients with severe renal impairment (CLCR≤30mL/min) and in patients with endstage renal disease. VIMPAT is effectively removed from plasma by hemodialysis. Following a 4-hour hemodialysis treatment, AUC of VIMPAT is reduced by approximately 50%. Therefore dosage supplementation of up to 50% following hemodialysis should be considered. In all renal impaired patients, the dose titration should be performed with caution. [see Dosage and Administration (2.2) and Clinical Pharmacology (12.3)]

8.7 Patients with Hepatic Impairment

Patients with mild to moderate hepatic impairment should be observed closely during dose titration. A maximum dose of 300 mg/day is recommended for patients with mild to moderate hepatic impairment. The pharmacokinetics of lacosamide has not been evaluated in severe hepatic impairment. VIMPAT use is not recommended in patients with severe hepatic impairment. [see Dosage and Administration (2.3) and Clinical Pharmacology (12.3)] Patients with co-existing hepatic and renal impairment should be monitored closely during dose titration.

9 DRUG ABUSE AND DEPENDENCE

9.1 Controlled Substance

VIMPAT is a Schedule V controlled substance.

9.2 Abuse

In a human abuse potential study, single doses of 200 mg and 800 mg lacosamide produced euphoria-type subjective responses that differentiated statistically from placebo; at 800 mg, these euphoria-type responses were statistically indistinguishable from those produced by alprazolam, a Schedule IV drug. The duration of the euphoria-type responses following lacosamide was less than that following alprazolam. A high rate of euphoria was also reported as an adverse event in the human abuse potential study following single doses of 800 mg lacosamide (15% [5/34]) compared to placebo (0%) and in two pharmacokinetic studies following single and multiple doses of 300-800 mg lacosamide (ranging from 6% [2/33] to 25% [3/12]) compared to placebo (0%). However, the rate of euphoria reported as an adverse event in the VIMPAT development program at therapeutic doses was less than 1%.

9.3 Dependence

Abrupt termination of lacosamide in clinical trials with diabetic neuropathic pain patients produced no signs or symptoms that are associated with a withdrawal syndrome indicative of physical dependence. However, psychological dependence cannot be excluded due to the ability of lacosamide to produce euphoria-type adverse events in humans.

10 OVERDOSAGE

10.1 Signs, Symptoms, and Laboratory Findings of Acute Overdose in Humans

There is limited clinical experience with VIMPAT overdose in humans. The highest reported accidental overdose of VIMPAT during clinical development was 1200 mg/day which was non-fatal. The types of adverse events experienced by patients exposed to supratherapeutic doses during the trials were not clinically different from those of patients administered recommended doses of VIMPAT.

There has been a single case of intentional overdose by a patient who self-administered 12 grams VIMPAT along with large doses of zonisamide, topiramate, and gabapentin. The patient presented in a coma and was hospitalized. An EEG revealed epileptic waveforms. The patient recovered 2 days later.

10.2 Treatment or Management of Overdose

There is no specific antidote for overdose with VIMPAT. Standard decontamination procedures should be followed. General supportive care of the patient is indicated including monitoring of vital signs and observation of the clinical status of patient. A Certified Poison Control Center should be contacted for up to date information on the management of overdose with VIMPAT.

Standard hemodialysis procedures result in significant clearance of VIMPAT (reduction of systemic exposure by 50% in 4 hours). Hemodialysis has not been performed in the few known cases of overdose, but may be indicated based on the patient's clinical state or in patients with significant renal impairment.

11 DESCRIPTION

The chemical name of lacosamide, the single (R)-enantiomer, is (R)-2-acetamido-N-benzyl-3-methoxypropionamide (IUPAC). Lacosamide is a functionalized amino acid. Its molecular formula is C13H18N2O3 and its molecular weight is 250.30. The chemical structure is:

Lacosamide is a white to light yellow powder. It is sparingly soluble in water and slightly soluble in acetonitrile and ethanol.

11.1 VIMPAT Tablets

VIMPAT tablets contain the following inactive ingredients: colloidal silicon dioxide, crospovidone, hydroxypropylcellulose, hypromellose, magnesium stearate, microcrystalline cellulose, polyethylene glycol, polyvinyl alcohol, talc, titanium dioxide, and dye pigments as specified below:

VIMPAT tablets are supplied as debossed tablets and contain the following coloring agents:

50 mg tablets: red iron oxide, black iron oxide, FD&C Blue #2/indigo carmine aluminum lake
100 mg tablets: yellow iron oxide
150 mg tablets: yellow iron oxide, red iron oxide, black iron oxide
200 mg tablets: FD&C Blue #2/indigo carmine aluminum lake

11.2 VIMPAT Injection

VIMPAT injection is a clear, colorless, sterile solution containing 10 mg lacosamide per mL for intravenous infusion. One 20-mL vial contains 200 mg of lacosamide drug substance. The inactive ingredients are sodium chloride and water for injection. Hydrochloric acid is used for pH adjustment. VIMPAT injection has a pH of 3.5 to 5.0.

11.3 VIMPAT Oral Solution

VIMPAT oral solution contains 10 mg of lacosamide per mL. The inactive ingredients are purified water, sorbitol solution, glycerin, polyethylene glycol, carboxymethylcellulose sodium, acesulfame potassium, methylparaben, flavoring (including natural and artificial flavors, propylene glycol, aspartame, and maltol), anhydrous citric acid and sodium chloride.

12 CLINICAL PHARMACOLOGY

12.1 Mechanism of Action

The precise mechanism by which VIMPAT exerts its antiepileptic effects in humans remains to be fully elucidated. In vitro electrophysiological studies have shown that lacosamide selectively enhances slow inactivation of voltage-gated sodium channels, resulting in stabilization of hyperexcitable neuronal membranes and inhibition of repetitive neuronal firing.

Lacosamide binds to collapsin response mediator protein-2 (CRMP-2), a phosphoprotein which is mainly expressed in the nervous system and is involved in neuronal differentiation and control of axonal outgrowth. The role of CRMP-2 binding in seizure control is unknown.

12.2 Pharmacodynamics

A pharmacokinetic-pharmacodynamic (efficacy) analysis was performed based on the pooled data from the 3 efficacy trials for partial-onset seizures. Lacosamide exposure is correlated with the reduction in seizure frequency. However, doses above 400 mg/day do not appear to confer additional benefit in group analyses.

Cardiac Electrophysiology

Electrocardiographic effects of VIMPAT were determined in a double-blind, randomized clinical pharmacology trial of 247 healthy subjects. Chronic oral doses of 400 and 800 mg/day were compared with placebo and a positive control (400 mg moxifloxacin). VIMPAT did not prolong QTc interval and did not have a dose-related or clinically important effect on QRS duration. VIMPAT produced a small, dose-related increase in mean PR interval. At steady-state, the time of the maximum observed mean PR interval corresponded with tmax. The placebo-subtracted maximum increase in PR interval (at tmax) was 7.3 ms for the 400 mg/day group and 11.9 ms for the 800 mg/day group. For patients who participated in the controlled trials, the placebo-subtracted mean maximum increase in PR interval for a 400 mg/day VIMPAT dose was 3.1 ms in patients with partial-onset seizures and 9.4 ms for patients with diabetic neuropathy.

12.3 Pharmacokinetics

The pharmacokinetics of VIMPAT have been studied in healthy adult subjects (age range 18 to 87), adults with partial-onset seizures, adults with diabetic neuropathy, and subjects with renal and hepatic impairment.

VIMPAT is completely absorbed after oral administration with negligible first-pass effect with a high absolute bioavailability of approximately 100%. The maximum lacosamide plasma concentrations occur approximately 1 to 4 hour post-dose after oral dosing, and elimination half-life is approximately 13 hours. Steady state plasma concentrations are achieved after 3 days of twice daily repeated administration. Pharmacokinetics of VIMPAT are dose proportional (100-800 mg) and time invariant, with low inter- and intra-subject variability. Compared to lacosamide the major metabolite, O-desmethyl metabolite, has a longer Tmax (0.5 to 12 hours) and elimination half-life (15-23 hours).

Absorption and Bioavailability

VIMPAT is completely absorbed after oral administration. The oral bioavailability of VIMPAT tablets is approximately 100%. Food does not affect the rate and extent of absorption.

After intravenous administration, Cmax is reached at the end of infusion. The 30- and 60-minute intravenous infusions are bioequivalent to the oral tablet.

In a trial comparing the oral tablet with and an oral solution containing 10 mg/mL lacosamide, bioequivalence between both formulations was shown.

Distribution

The volume of distribution is approximately 0.6 L/kg and thus close to the volume of total body water. VIMPAT is less than 15% bound to plasma proteins.

Metabolism and Elimination

VIMPAT is primarily eliminated from the systemic circulation by renal excretion and biotransformation.

After oral and intravenous administration of 100 mg [14C]-lacosamide approximately 95% of radioactivity administered was recovered in the urine and less than 0.5% in the feces. The major compounds excreted were unchanged lacosamide (approximately 40% of the dose), its O-desmethyl metabolite (approximately 30%), and a structurally unknown polar fraction (~20%). The plasma exposure of the major human metabolite, O-desmethyl-lacosamide, is approximately 10% of that of lacosamide. This metabolite has no known pharmacological activity.

Lacosamide is a CYP2C19 substrate. The relative contribution of other CYP isoforms or non-CYP enzymes in the metabolism of lacosamide is not clear. The elimination half-life of the unchanged drug is approximately 13 hours and is not altered by different doses, multiple dosing or intravenous administration.

There is no enantiomeric interconversion of lacosamide.

Special Populations

Renal impairment

Lacosamide and its major metabolite are eliminated from the systemic circulation primarily by renal excretion.

The AUC of VIMPAT was increased approximately 25% in mildly (CLCR 50-80 mL/min) and moderately (CLCR 30-50 mL/min) and 60% in severely (CLCR≤30mL/min) renally impaired patients compared to subjects with normal renal function (CLCR>80mL/min), whereas Cmax was unaffected. No dose adjustment is considered necessary in mildly and moderately renal impaired subjects. A maximum dose of 300 mg/day is recommended for patients with severe renal impairment (CLCR≤30mL/min) and in patients with endstage renal disease. VIMPAT is effectively removed from plasma by hemodialysis. Following a 4-hour hemodialysis treatment, AUC of VIMPAT is reduced by approximately 50%. Therefore dosage supplementation of up to 50% following hemodialysis should be considered. In all renal impaired patients, the dose titration should be performed with caution. [see Dosage and Administration (2.3)]

Hepatic impairment

Lacosamide undergoes metabolism. Subjects with moderate hepatic impairment (Child-Pugh B) showed higher plasma concentrations of lacosamide (approximately 50-60% higher AUC compared to healthy subjects). The dose titration should be performed with caution in patients with hepatic impairment. A maximum dose of 300 mg/day is recommended for patients with mild or moderate hepatic impairment.

Patients with mild to moderate hepatic impairment should be observed closely during dose titration. A maximum dose of 300 mg/day is recommended for patients with mild to moderate hepatic impairment. The pharmacokinetics of lacosamide have not been evaluated in severe hepatic impairment. VIMPAT use is not recommended in patients with severe hepatic impairment. [see Dosage and Administration (2.3)] Patients with co-existing hepatic and renal impairment should be monitored closely during dose titration.

Geriatric

In the elderly (>65 years), dose and body-weight normalized AUC and Cmax is about 20% increased compared to young subjects (18-64 years). This may be related to body weight and decreased renal function in elderly subjects. Dose reduction is not considered to be necessary.

Pediatric Patients

Pharmacokinetics of VIMPAT have not been studied in pediatric patients.

Gender

VIMPAT clinical trials indicate that gender does not have a clinically relevant influence on the pharmacokinetics of VIMPAT.

Race

There are no clinically relevant differences in the pharmacokinetics of VIMPAT between Asian, Black, and Caucasian subjects.

CYP2C19 Polymorphism

There are no clinically relevant differences in the pharmacokinetics of VIMPAT between CYP2C19 poor metabolizers and extensive metabolizers. Results from a trial in poor metabolizers (PM) (N=4) and extensive metabolizers (EM) (N=8) of cytochrome P450 (CYP) 2C19 showed that lacosamide plasma concentrations were similar in PMs and EMs, but plasma concentrations and the amount excreted into urine of the O-desmethyl metabolite were about 70% reduced in PMs compared to EMs.

Drug interactions

In Vitro Assessment of Drug Interactions

In vitro metabolism studies indicate that lacosamide does not induce the enzyme activity of drug metabolizing cytochrome P450 isoforms CYP1A2, 2B6, 2C9, 2C19 and 3A4. Lacosamide did not inhibit CYP 1A1, 1A2, 2A6, 2B6, 2C8, 2C9, 2D6, 2E1, 3A4/5 at plasma concentrations observed in clinical studies.

In vitro data suggest that lacosamide has the potential to inhibit CYP2C19 at therapeutic concentrations. However, an in vivo study with omeprazole did not show an inhibitory effect on omeprazole pharmacokinetics.

Lacosamide was not a substrate or inhibitor for P-glycoprotein.

Lacosamide is a CYP2C19 substrate. The relative contribution of other CYP isoforms or non-CYP enzymes in the metabolism of lacosamide is not clear.

Since <15% of lacosamide is bound to plasma proteins, a clinically relevant interaction with other drugs through competition for protein binding sites is unlikely.

Drug interaction studies with AEDs

Effect of VIMPAT on concomitant AEDs: VIMPAT 400 mg/day had no influence on the pharmacokinetics of 600 mg/day valproic acid and 400 mg/day carbamazepine in healthy subjects.

The placebo-controlled clinical studies in patients with partial-onset seizures showed that steady-state plasma concentrations of levetiracetam, carbamazepine, carbamazepine epoxide, lamotrigine, topiramate, oxcarbazepine monohydroxy derivative (MHD), phenytoin, valproic acid, phenobarbital, gabapentin, clonazepam, and zonisamide were not affected by concomitant intake of VIMPAT at any dose.

Effect of concomitant AEDs on VIMPAT: Drug-drug interaction studies in healthy subjects showed that 600 mg/day valproic acid had no influence on the pharmacokinetics of 400 mg/day VIMPAT. Likewise, 400 mg/day carbamazepine had no influence on the pharmacokinetics of VIMPAT in a healthy subject study. Population pharmacokinetics results in patients with partial-onset seizures showed small reductions (15% to 20% lower) in lacosamide plasma concentrations when VIMPAT was coadministered with carbamazepine, phenobarbital or phenytoin.

Drug-drug interaction studies with other drugs

Digoxin

There was no effect of VIMPAT (400 mg/day) on the pharmacokinetics of digoxin (0.5 mg once daily) in a study in healthy subjects.

Metformin

There were no clinically relevant changes in metformin levels following coadministration of VIMPAT (400 mg/day).

Metformin (500 mg three times a day) had no effect on the pharmacokinetics of VIMPAT (400 mg/day).

Omeprazole

Omeprazole is a CYP2C19 substrate and inhibitor.

There was no effect of VIMPAT (600 mg/day) on the pharmacokinetics of omeprazole (40 mg single dose) in healthy subjects. The data indicated that lacosamide had little in vivo inhibitory or inducing effect on CYP2C19.

Omeprazole at a dose of 40 mg once daily had no effect on the pharmacokinetics of VIMPAT (300 mg single dose). However, plasma levels of the O-desmethyl metabolite were reduced about 60% in the presence of omeprazole.

Oral Contraceptives

There was no influence of VIMPAT (400 mg/day) on the pharmacodynamics and pharmacokinetics of an oral contraceptive containing 0.03 mg ethinylestradiol and 0.15 mg levonorgestrel in healthy subjects, except that a 20% increase in ethinylestradiol Cmax was observed.

13 NONCLINICAL TOXICOLOGY

13.1 Carcinogenesis, Mutagenesis, Impairment of Fertility

There was no evidence of drug related carcinogenicity in mice or rats. Mice and rats received lacosamide once daily by oral administration for 104 weeks at doses producing plasma exposures (AUC) up to approximately 1 and 3 times, respectively, the plasma AUC in humans at the maximum recommended human dose (MRHD) of 400 mg/day.

Lacosamide was negative in an in vitro Ames test and an in vivo mouse micronucleus assay. Lacosamide induced a positive response in the in vitro mouse lymphoma assay.

No adverse effects on male or female fertility or reproduction were observed in rats at doses producing plasma exposures (AUC) up to approximately 2 times the plasma AUC in humans at the MRHD.

14 CLINICAL STUDIES

14.1 Effectiveness in Partial-Onset Seizures

The efficacy of VIMPAT as adjunctive therapy in partial-onset seizures was established in three 12-week, randomized, double-blind, placebo-controlled, multicenter trials in adult patients. Patients enrolled had partial-onset seizures with or without secondary generalization and were not adequately controlled with 1 to 3 concomitant AEDs. During an 8-week baseline period, patients were required to have an average of ≥4 partial-onset seizures per 28 days with no seizure-free period exceeding 21 days. In these 3 trials, patients had a mean duration of epilepsy of 24 years and a median baseline seizure frequency ranging from 10 to 17 per 28 days. 84% of patients were taking 2 to 3 concomitant AEDs with or without concurrent vagal nerve stimulation.

Study 1 compared doses of VIMPAT 200, 400, and 600 mg/day with placebo. Study 2 compared doses of VIMPAT 400 and 600 mg/day with placebo. Study 3 compared doses of VIMPAT 200 and 400 mg/day with placebo. In all three trials, following an 8-week Baseline Phase to establish baseline seizure frequency prior to randomization, subjects were randomized and titrated to the randomized dose (a 1-step back-titration of VIMPAT 100 mg/day or placebo was allowed in the case of intolerable adverse events at the end of the Titration Phase). During the Titration Phase in all 3 trials, treatment was initiated at 100 mg/day (50 mg given twice daily) and increased in weekly increments of 100 mg/day to the target dose. The Titration Phase lasted 6 weeks in Study 1 and Study 2 and 4 weeks in Study 3. In all three trials, the Titration Phase was followed by a Maintenance Phase that lasted 12 weeks, during which patients were to remain on a stable dose of VIMPAT.

A reduction in 28 day seizure frequency (Baseline to Maintenance Phase) as compared to the placebo group was the primary variable in all three trials. The criteria for statistical significance was p<0.05. A statistically significant effect was observed with VIMPAT treatment (Figure 1) at doses of 200 mg/day (Study 3), 400 mg/day (Studies 1, 2, and 3), and 600 mg/day (Studies 1 and 2).

Subset evaluations of VIMPAT demonstrate no important differences in seizure control as a function of gender or race, although data on race was limited (about 10% of patients were non-Caucasian).

Figure 2 presents the percentage of patients (X-axis) with a percent reduction in partial seizure frequency (responder rate) from Baseline to the Maintenance phase at least as great as that represented on the Y-axis. A positive value on the Y-axis indicates an improvement from Baseline (i.e., a decrease in seizure frequency), while a negative value indicates a worsening from Baseline (ie., an increase in seizure frequency). Thus, in a display of this type, a curve for an effective treatment is shifted to the left of the curve for placebo. The proportion of patients achieving any particular level of reduction in seizure frequency was consistently higher for the VIMPAT groups compared to the placebo group. For example, 40% of patients randomized to VIMPAT (400 mg/day) experienced a 50% or greater reduction in seizure frequency, compared to 23% of patients randomized to placebo. Patients with an increase in seizure frequency >100% are represented on the Y-axis as equal to or greater than -100%.

16 HOW SUPPLIED/STORAGE AND HANDLING

VIMPAT (lacosamide) Tablets 50 mg are pink, oval, film-coated tablets debossed with "SP" on one side and "50" on the other. They are supplied as follows:

Bottles of 60 | NDC54868-6077-0

16.1 Storage

Store at 20° to 25°C (68° to 77°F); excursions permitted between 15° to 30°C (59° to 86°F). [See USP Controlled Room Temperature].

Do not freeze Vimpat injection or oral solution. Discard any unused Vimpat oral solution remaining after seven (7) weeks of first opening the bottle.

17 PATIENT COUNSELING INFORMATION

[See Medication Guide]

Patients should be informed of the availability of a Medication Guide, and they should be instructed to read the Medication Guide prior to taking VIMPAT. Patients should be instructed to take VIMPAT only as prescribed.

17.1 Suicidal Thinking and Behavior

Patients, their caregivers, and families should be counseled that AEDs, including VIMPAT, may increase the risk of suicidal thoughts and behavior and should be advised of the need to be alert for the emergence or worsening of symptoms of depression, any unusual changes in mood or behavior, or the emergence of suicidal thoughts, behavior, or thoughts about self-harm. Behaviors of concern should be reported immediately to healthcare providers.

17.2 Dizziness and Ataxia

Patients should be counseled that VIMPAT use may cause dizziness, double vision, abnormal coordination and balance, and somnolence. Patients taking VIMPAT should be advised not to drive, operate complex machinery, or engage in other hazardous activities until they have become accustomed to any such effects associated with VIMPAT.

17.3 Cardiac Rhythm and Conduction Abnormalities

Patients should be counseled that VIMPAT is associated with electrocardiographic changes that may predispose to irregular beat and syncope, particularly in patients with underlying cardiovascular disease, with heart conduction problems or who are taking other medications that affect the heart. Patients who develop syncope should lay down with raised legs until recovered and contact their health care provider.

17.4 Multiorgan Hypersensitivity Reactions

Patients should be aware that VIMPAT may cause serious hypersensitivity reactions affecting multiple organs such as the liver and kidney. VIMPAT should be discontinued if a serious hypersensitivity reaction is suspected. Patients should also be instructed to report promptly to their physicians any symptoms of liver toxicity (e.g. fatigue, jaundice, dark urine).

17.5 Pregnancy Registry

UCB, Inc. has established the UCB AED Pregnancy Registry to advance scientific knowledge about safety and outcomes in pregnant women being treated with VIMPAT. To ensure broad program access and reach, either a healthcare provider or the patient can initiate enrollment in the UCB AED Pregnancy Registry by calling 1-888-537-7734 (toll free).

Patients should also be encouraged to enroll in the North American Antiepileptic Drug Pregnancy Registry if they become pregnant. This Registry is collecting information about the safety of AEDs during pregnancy. To enroll, patients can call the toll free number 1-888-233-2334 [see Use in Specific Populations (8.1)].

Medication Guide

VIMPAT (VIM-păt) CV

(lacosamide)

Tablet, Oral Solution and Injection for Intravenous Use

Read this Medication Guide before you start taking VIMPAT and each time you get a refill. There may be new information. This Medication Guide describes important safety information about VIMPAT. This information does not take the place of talking to your healthcare provider about your medical condition or treatment.

What is the most important information I should know about VIMPAT?

Do not stop taking VIMPAT without first talking to your healthcare provider.

Stopping VIMPAT suddenly can cause serious problems.

VIMPAT can cause serious side effects, including:

1. Like other antiepileptic drugs, VIMPAT may cause suicidal thoughts or actions in a very small number of people, about 1 in 500.
  Call a healthcare provider right away if you have any of these symptoms, especially if they are new, worse, or worry you:
  - thoughts about suicide or dying
  - attempt to commit suicide
  - new or worse depression
  - new or worse anxiety
  - feeling agitated or restless
  - panic attacks
  - trouble sleeping (insomnia)
  - new or worse irritability
  - acting aggressive, being angry, or violent
  - acting on dangerous impulses
  - an extreme increase in activity and talking (mania)
  - other unusual changes in behavior or mood
  How can I watch for early symptoms of suicidal thoughts and actions?
  - Pay attention to any changes, especially sudden changes, in mood, behaviors, thoughts, or feelings.
  - Keep all follow-up visits with your healthcare provider as scheduled.
  - Call your healthcare provider between visits as needed, especially if you are worried about symptoms.
  - Suicidal thoughts or actions can be caused by things other than medicines. If you have suicidal thoughts or actions, your healthcare provider may check for other causes.
  - Do not stop VIMPAT without first talking to a healthcare provider. Stopping VIMPAT suddenly can cause serious problems. Stopping seizure medicine suddenly in a patient who has epilepsy can cause seizures that will not stop (status epilepticus).
2. Vimpat may cause you to feel dizzy, have double vision, feel sleepy, or have problems with coordination and walking. Do not drive, operate heavy machinery, or do other dangerous activities until you know how VIMPAT affects you.
3. VIMPAT may cause you to have an irregular heartbeat or may cause you to faint. Call your healthcare provider if you have:
  - fast, slow, or pounding heartbeat
  - shortness of breath
  - feel lightheaded
  - fainted or if you feel like you are going to faint
  If you have fainted or feel like you are going to faint you should lay down with your legs raised until you feel better.
4. VIMPAT is a federally controlled substance (C-V) because it can be abused or lead to drug dependence. Keep your VIMPAT in a safe place, to protect it from theft. Never give your VIMPAT to anyone else, because it may harm them. Selling or giving away this medicine is against the law.

What is VIMPAT?

VIMPAT is a prescription medicine used with other medicines to treat partial-onset seizures in people 17 years of age and older.

What should I tell my healthcare provider before taking VIMPAT?

Before you take VIMPAT, tell your healthcare provider, if you:

- have or have had depression, mood problems or suicidal thoughts or behavior
- have heart problems
- have kidney problems
- have liver problems
- have abused prescription medicines, street drugs or alcohol in the past
- have any other medical problems
- are pregnant or plan to become pregnant. It is not known if VIMPAT can harm your unborn baby. Tell your healthcare provider right away if you become pregnant while taking VIMPAT. You and your healthcare provider will decide if you should take VIMPAT while you are pregnant.
  - If you become pregnant while taking VIMPAT, talk to your healthcare provider about registering with the North American Antiepileptic Drug Pregnancy Registry. You can enroll in this registry by calling 1-888-233-2334. You can also enroll in the UCB AED Pregnancy Registry by calling 1-888-537-7734. The purpose of this registry is to collect information about the safety of antiepileptic medicine during pregnancy.
- are breastfeeding or plan to breastfeed. It is not known if VIMPAT passes into your breast milk or if it can harm your baby. Talk to your healthcare provider about the best way to feed your baby if you take VIMPAT.

Tell your healthcare provider about all the medicines you take, including prescription and non-prescription medicines, vitamins, and herbal supplements.

Taking VIMPAT with certain other medicines may cause side effects or affect how they work. Do not start or stop other medicines without talking to your healthcare provider. Know the medicines you take. Keep a list of them and show it to your healthcare provider and pharmacist each time you get a new medicine.

How should I take VIMPAT?

- Take VIMPAT exactly as your healthcare provider tells you.
- Your healthcare provider will tell you how much VIMPAT to take and when to take it.
- Your healthcare provider may change your dose if needed.
- Do not stop VIMPAT without first talking to a healthcare provider. Stopping VIMPAT suddenly in a patient who has epilepsy can cause seizures that will not stop (status epilepticus).
- VIMPAT may be taken with or without food.
- If your healthcare provider has prescribed VIMPAT oral solution, be sure to ask your pharmacist for a medicine dropper or medicine cup to help you measure the correct amount of VIMPAT oral solution. Do not use a household teaspoon. Ask your pharmacist for instructions on how to use the measuring device the right way.
- If you take too much VIMPAT, call your healthcare provider or local Poison Control Center right away.

What should I avoid while taking VIMPAT?

Do not drive, operate heavy machinery, or do other dangerous activities until you know how VIMPAT affects you. VIMPAT may cause you to feel dizzy, have double vision, feel sleepy, or have problems with coordination and walking.

What are the possible side effects of VIMPAT?

See "What is the most important information I should know about VIMPAT?".

VIMPAT may cause other serious side effects including:

VIMPAT may cause a serious allergic reaction that may affect your skin or other parts of your body such as your liver or blood cells. Call your healthcare provider right away if you have:

- a skin rash, hives
- fever or swollen glands that do not go away
- shortness of breath, swelling of the legs, yellowing of the skin or whites of the eyes, or dark urine.

The most common side effects of VIMPAT include:

- dizziness
- headache
- double vision
- nausea

These are not all of the possible side effects of VIMPAT. For more information ask your healthcare provider or pharmacist. Tell your healthcare provider about any side effect that bothers you or that does not go away. Call your healthcare provider for medical advice about side effects. You may report side effects to FDA at 1-800-FDA-1088.

How should I store VIMPAT?

- Store VIMPAT between 59° F to 86° F (15° C to 30° C)

Keep VIMPAT and all medicines out of the reach of children

General Information about VIMPAT

Medicines are sometimes prescribed for purposes other than those listed in a Medication Guide. Do not use VIMPAT for a condition for which it was not prescribed. Do not give VIMPAT to other people, even if they have the same symptoms you have. It may harm them.

This Medication Guide summarizes the most important information about VIMPAT. If you would like more information, talk with your healthcare provider. You can ask your pharmacist or healthcare provider for information about VIMPAT that is written for health professionals.

For more information, go to www.vimpat.com or call 1-800-477-7877.

What are the ingredients in VIMPAT?

Active ingredient: lacosamide
Tablet inactive ingredients: colloidal silicon dioxide, crospovidone, hydroxypropylcellulose, hypromellose, magnesium stearate, microcrystalline cellulose, polyethylene glycol, polyvinyl alcohol, talc, titanium dioxide and additional ingredients listed below:
  - 50 mg tablets: red iron oxide, black iron oxide, FD&C Blue #2/indigo carmine aluminum lake
  - 100 mg tablets: yellow iron oxide
  - 150 mg tablets: yellow iron oxide, red iron oxide, black iron oxide
  - 200 mg tablets: FD&C Blue #2/indigo carmine aluminum lake
Oral solution inactive ingredients: purified water, sorbitol solution, glycerin, polyethylene glycol, carboxymethylcellulose sodium, acesulfame potassium, methylparaben, flavoring (including natural and artificial flavors, propylene glycol, aspartame, and maltol), anhydrous citric acid and sodium chloride.
Injection inactive ingredients: sodium chloride, water for injection, hydrochloric acid

Manufactured for
UCB, Inc.
Smyrna, GA 30080

Issued 04/2011

This Medication Guide has been approved by the U.S. Food and Drug Administration.

VIMPAT® is a registered trademark under license from Harris FRC Corporation and covered by one or more claims of U.S. Patent 38,551.

Additional barcode labeling by:
Physicians Total Care, Inc.
Tulsa, Oklahoma 74146

PRINCIPAL DISPLAY PANEL - 50 mg Tablet Bottle Label

NDC 54868-6077-0

VIMPAT®
(lacosamide) tablets
CV

50 mg

Rx only
60 Tablets

ATTENTION PHARMACIST:
Each patient is required to receive the
accompanying Medication Guide.